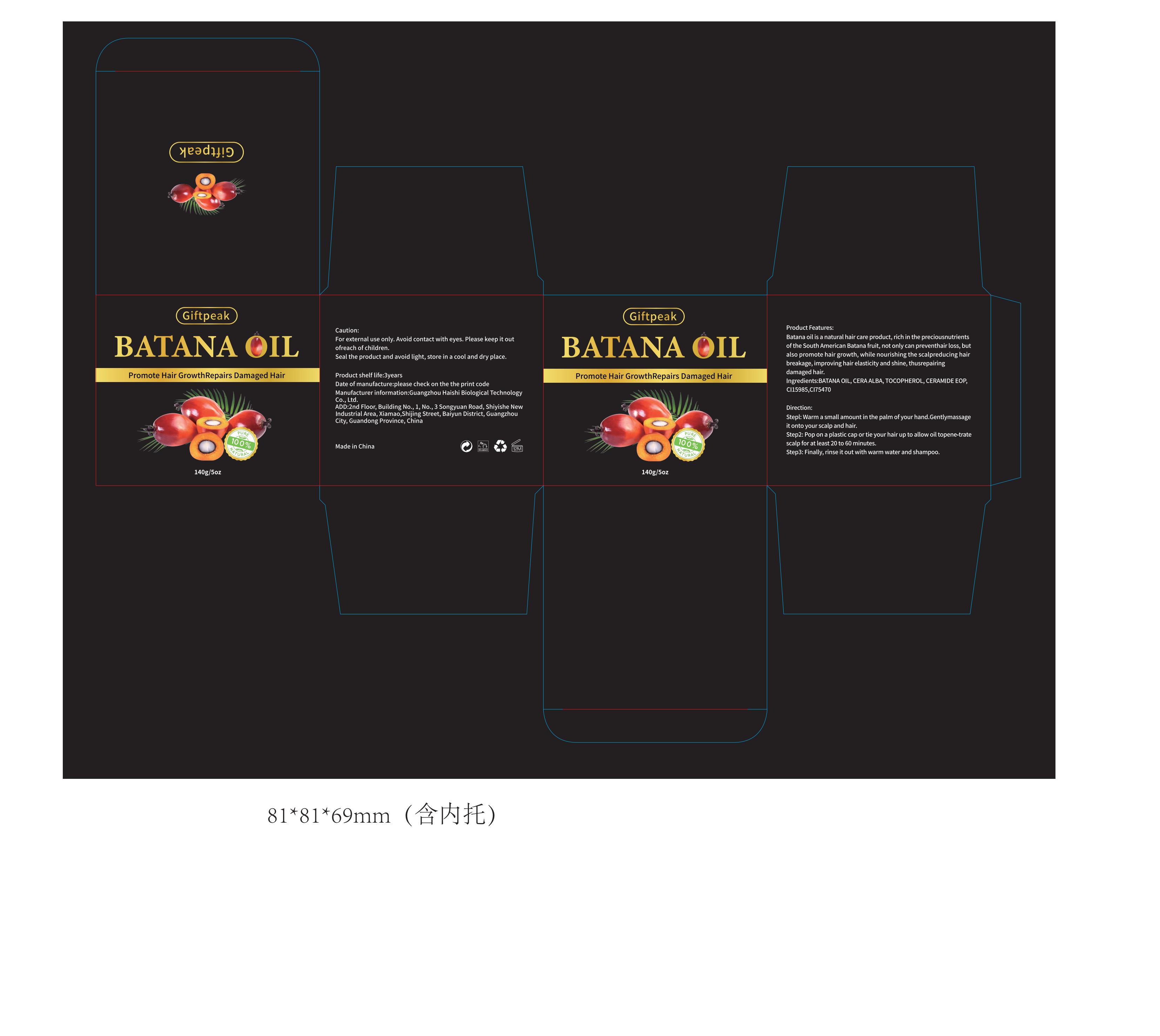 DRUG LABEL: Giftpeak batana oil
NDC: 60771-0002 | Form: OINTMENT
Manufacturer: Guangzhou Haishi Biological Technology Co., Ltd.
Category: otc | Type: HUMAN OTC DRUG LABEL
Date: 20241008

ACTIVE INGREDIENTS: PALM OIL 92.96421 g/100 g; TOCOPHEROL 2 g/100 g
INACTIVE INGREDIENTS: PEG-8 BEESWAX

Giftpeak BATANA OIL

Active ingredients

BATANA OIL 92.96421%

TOCOPHEROL 2%

Purpose

Hair growth

Uses

Step1: Warm a small amount in the palm ofyour hand.Gentlymassageit onto your scalp and hair.
Step2: Pop on a plastic cap or tie your hair up to allow oil topene-tratescalp for at least 20 to 60 minutes.
Step3: Finally, rinse it out with warm water and shampoo.

Warnings

For external use only.

Stop use and ask a doctor if

rash occurs.

Do not use

on damaged or broken skin.

When using this product

keep out of eyes. Rinse with water to remove.

Keep out of reach of children.

If swallowed, get medical help or contact a Poison Control Center right away.

Dosage

Squeeze out an appropriate amount of product and spread evenly on skin.

Inactive ingredients

CERA ALBA 5%

CI 15985 0.0278%

CI 75470 0.00559%